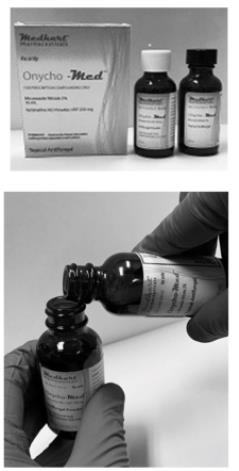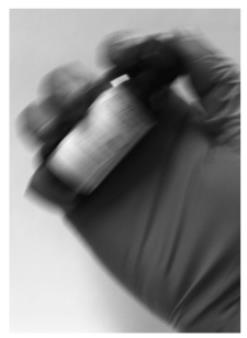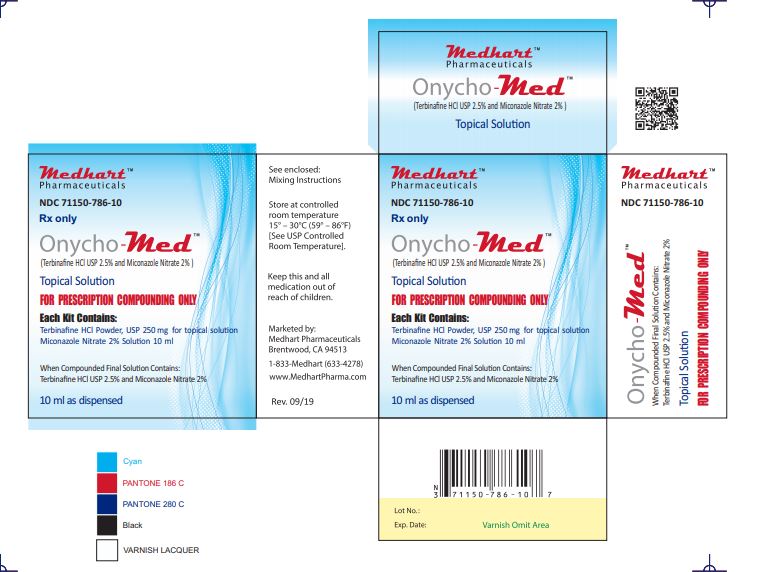 DRUG LABEL: Onycho-Med
NDC: 71150-786 | Form: KIT | Route: TOPICAL
Manufacturer: Medhart Pharmaceuticals, Inc.
Category: prescription | Type: HUMAN PRESCRIPTION DRUG LABEL
Date: 20230116

ACTIVE INGREDIENTS: TERBINAFINE HYDROCHLORIDE 250 mg/10 mL; MICONAZOLE NITRATE 200 mg/10 mL
INACTIVE INGREDIENTS: RIBOPRINE; ACETIC ACID; WATER; BENZYL ALCOHOL; DIMETHYL SULFOXIDE; LAURETH-4; POLYETHYLENE GLYCOL 300; TEA TREE OIL

Onycho-Med

Thank you for choosing Onycho-Med by Medhart Pharmaceuticals, Inc.

To the licensed medical professionals:

“This convenience kit is for prescription compounding only”

Please make sure the kit contains the following components:

Active Ingredients:

One Miconazole Nitrate USP 2% solution in 10ml bottle fitted with a brush cap lid One bottle containing 250 mgs of Terbinafine Hcl USP powder

In-Active Ingredients:

Acetic Acid, Aqua, Benzyl Alcohol, DMSO, IPA 70%, Laureth-4, PEG-6, Tea Tree Oil

How supplied:

Onycho-Med is a prescription only convenience kit for compounding by a healthcare professional for topical application in management of onychomycosis. The package contains premeasured bottles of Miconazole Nitrate 2% solution * and Terbinafine Hcl USP 250 mg** to make a final volume of 10 ml solution of Miconazole Nitrate 2% and Terbinafine Hcl USP 2.5%.

Indication:

Prescribed for the management of onychomycosis

Mixing Instructions - Easy Two Step Process

- Please check expiration dates listed on the bottles
- Inspect product integrity seals on the bottles inside the carton
- Take the bottles out of the carton and set aside the carton, as illustrated in the picture to the left
- Open the black brush-cap lid on the Miconazole Nitrate 2% bottle and place it aside for re-use
- Carefully un-screw the white cap from the Terbinafine Hcl 250mg bottle and set aside to discard later
- Carefully pour the contents of the bottle labelled Miconazole Nitrate 2% into the bottle labelled Terbinafine Hcl powder 250mg
- Place the black brush-cap lid on the Terbinafine Hcl 250mg bottle, that now has Miconazole Nitrate 2% in it as well and tighten the lid

To the licensed medical professionals:

“This convenience kit is for prescription compounding only”

- Now shake the bottle containing Terbinaﬁne Hcl 250mg USP powder and Miconazole Nitrate 2% solution vigorously for 30 seconds
- Make sure the contents have dissolved and there is no residue
- Apply the pharmacy label to the bottle with ﬁnal solution
- Place the ﬁnal solution (bottle with black brush cap) back into the carton
- Discard the empty bottle of Miconazole Nitrate 2% and the white cap appropriately
- Please instruct the patient to “shake well before use”

The non-compounded kit has a shelf-life of two years, The ﬁnal product once mixed will follow a 30 day expiration as per USP 795 BUD (Beyond Use Date) guidelines. Healthcare professionals please follow your local state board of pharmacy BUD guidelines as well. Please discard any unused components of the kit appropriately. Miconazole Nitrate 2% solution meets the requirements for total aerobic microbial count of no more than 100 cfu/gm, as well as for absence of the speciﬁed microorganisms Escherichia coli, Pseudomonas aeruginosa, Staphylococcus aureus, Salmonella and Candida albicans.

Storage:

The convenience kit and the compounded product can be stored at room temperature between (15 – 30^0c) and after compounding should be discarded after 30 days as per USP 795 guidelines. Protect from light, protect from freezing.

Onycho-Med compounding kit components have a two-year expiration date ***

For External Use Only: Keep container tightly closed, keep out of reach of children, and avoid contact with eyes.

* This product is not manufactured by Valeant Pharma manufacturers of Fungoid tincture

** Certificate of Analysis on file

***Data and documentation on ﬁle

Users are encouraged to report adverse events to FDA MedWatch

1-800-FDA-1088 or at http://www.fda.gov/Safety/MedWatch/HowToReport/ucm053074.htm

RX Only

Revised: April2019

Dear professionals we always value your feedback, please email at: suggestions@medhartpharma.com

Manufactured for:

Medhart Pharmaceuticals, Inc.

50 Eagle Rock Way, Suite C, Brentwood Ca 94513

Ph: 1-833-MEDHART (633-4278)

PRINCIPAL DISPLAY PANEL

NDC 71150-0786-10
Rx Only
Onycho-Med
(Terbinafine Hcl USP 2.5% and Miconazole Nitrate 2%)
FOR PRESCRIPTION COMPOUNDING ONLY
Topical Antifungal Solution